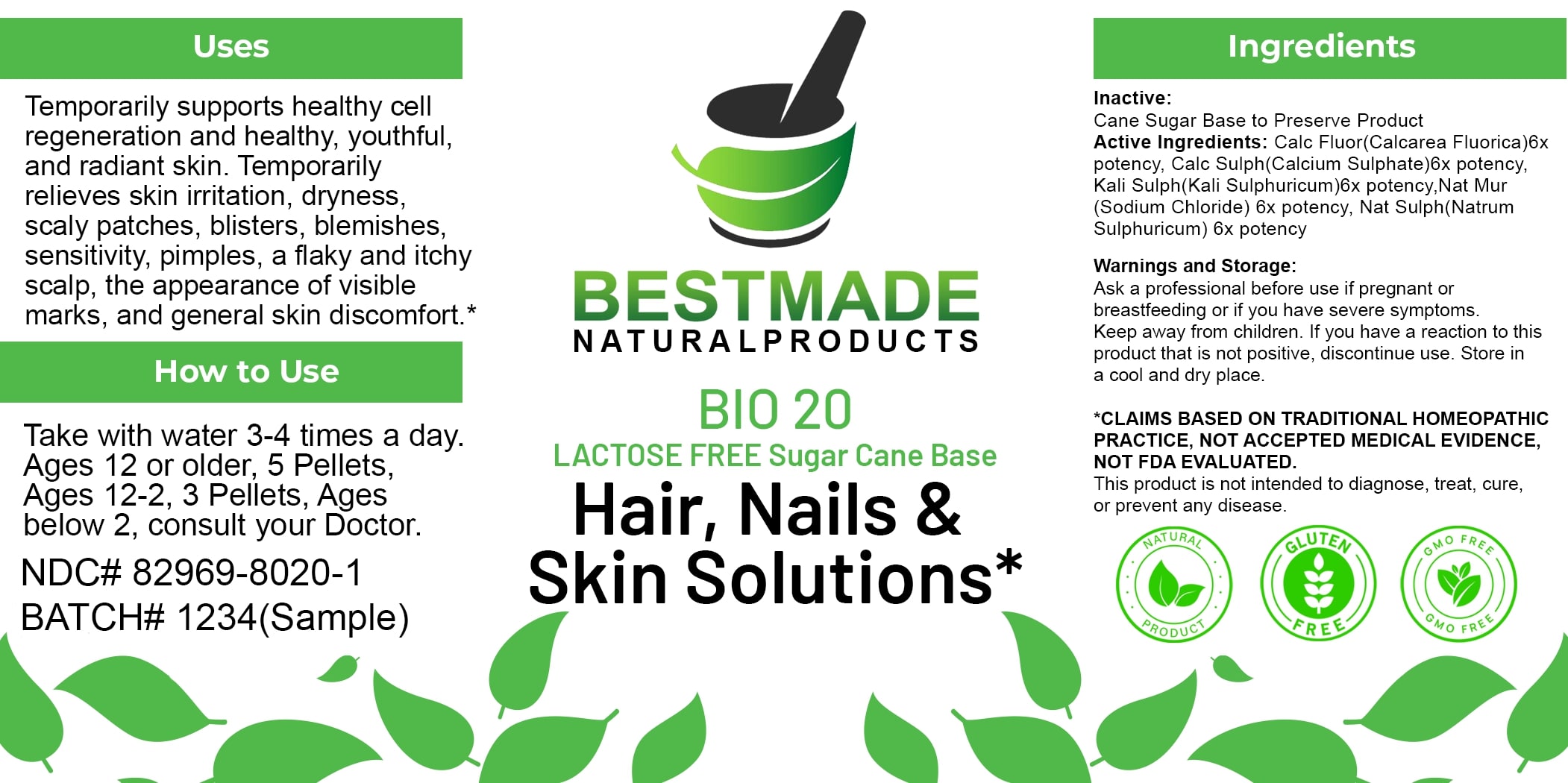 DRUG LABEL: Bestmade Natural Products BIO20 Lactose Free
NDC: 82969-8020 | Form: TABLET, SOLUBLE
Manufacturer: Bestmade Natural Products
Category: homeopathic | Type: HUMAN OTC DRUG LABEL
Date: 20250313

ACTIVE INGREDIENTS: CALCIUM SULFATE ANHYDROUS 6 [hp_X]/6 [hp_X]; SODIUM CHLORIDE 6 [hp_X]/6 [hp_X]; POTASSIUM SULFATE 6 [hp_X]/6 [hp_X]; SODIUM SULFATE 6 [hp_X]/6 [hp_X]; CALCIUM FLUORIDE 6 [hp_X]/6 [hp_X]
INACTIVE INGREDIENTS: SUCROSE 6 [hp_X]/6 [hp_X]

BIO20 Hair, Nails & Skin Solutions* LACTOSE FREE Sugar Cane Base

DOSAGE AND ADMINISTRATION

How to Use

Take with water 3-4 times a day. Ages 12 or older, 5 Pellets, Ages 12-2, 3 Pellets, Ages below 2, consult your Doctor.

Inactive:

Cane Sugar Base to Preserve Product

Active Ingredients:

Calc Fluor (Calcarea Fluorica) 6x potency, Calc Sulph (Calcium Sulphate) 6x potency, Kali Sulph (Kali Sulphuricum) 6x potency, Nat Mur (Sodium Chloride) 6x potency, Nat Sulph (Natrum Sulphuricum) 6x potency

Uses

Temporarily supports healthy cell regeneration and healthy, youthful, and radiant skin. Temporarily relieves skin irritation, dryness, scaly patches, blisters, blemishes, sensitivity, pimples, a flaky and itchy scalp, the appearance of visible marks, and general skin discomfort.*

*CLAIMS BASED ON TRADITIONAL HOMEOPATHIC PRACTICE, NOT ACCEPTED MEDICAL EVIDENCE, NOT FDA EVALUATED.

This product is not intended to diagnose, treat, cure, or prevent any disease.

Uses

Temporarily supports healthy cell regeneration and healthy, youthful, and radiant skin. Temporarily relieves skin irritation, dryness, scaly patches, blisters, blemishes, sensitivity, pimples, a flaky and itchy scalp, the appearance of visible marks, and general skin discomfort.*

*CLAIMS BASED ON TRADITIONAL HOMEOPATHIC PRACTICE, NOT ACCEPTED MEDICAL EVIDENCE, NOT FDA EVALUATED.

This product is not intended to diagnose, treat, cure, or prevent any disease.

KEEP OUT OF REACH OF CHILDREN

Warnings and Storage:

Ask a professional before use if pregnant or breastfeeding or if you have severe symptoms. Keep away from children. If you have a reaction to this product that is not positive, discontinue use. Store in a cool and dry place.

Warnings and Storage:

Ask a professional before use if pregnant or breastfeeding or if you have severe symptoms. Keep away from children. If you have a reaction to this product that is not positive, discontinue use. Store in a cool and dry place.

*CLAIMS BASED ON TRADITIONAL HOMEOPATHIC PRACTICE, NOT ACCEPTED MEDICAL EVIDENCE NOT FDA EVALUATED.

This product is not intended to diagnose, treat, cure, or prevent any disease.

Entire package label